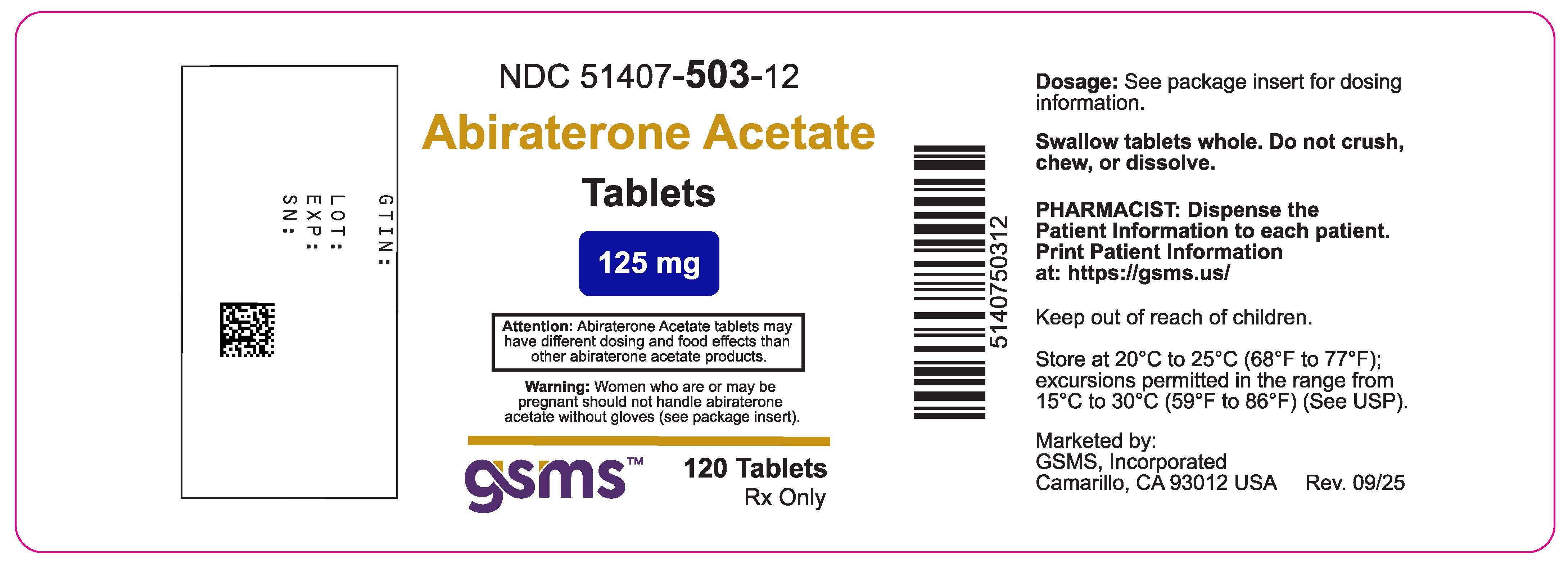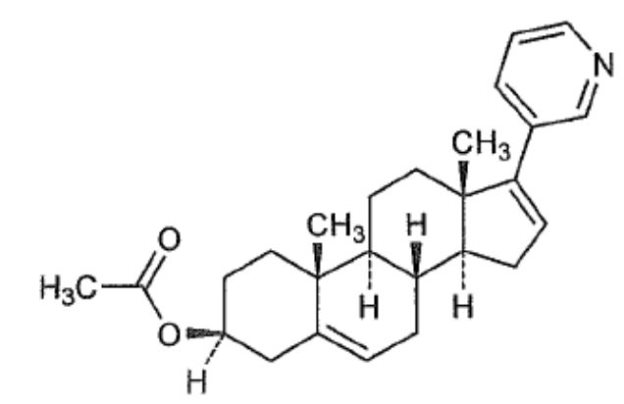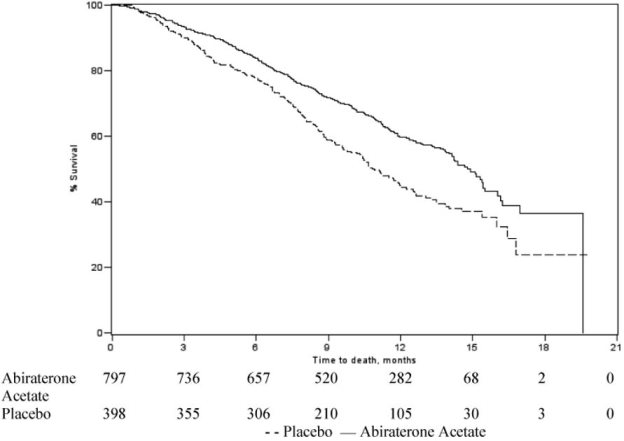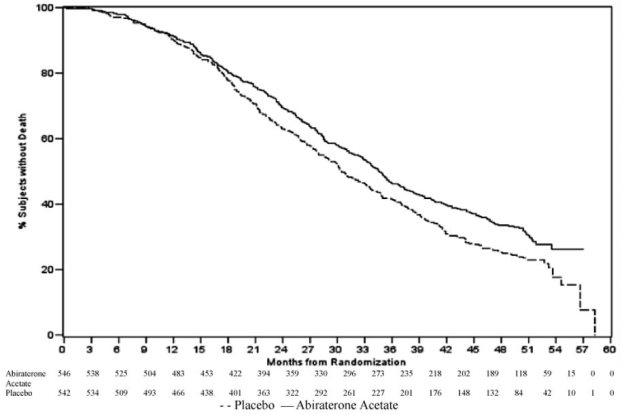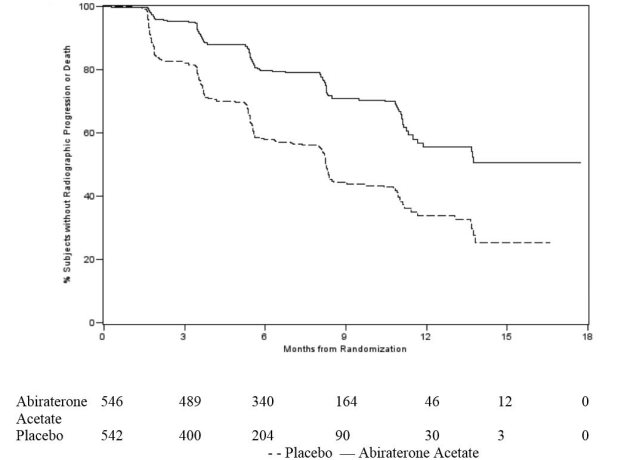 DRUG LABEL: Abiraterone Acetate
NDC: 51407-503 | Form: TABLET
Manufacturer: Golden State Medical Supply, Inc.
Category: prescription | Type: HUMAN PRESCRIPTION DRUG LABEL
Date: 20260120

ACTIVE INGREDIENTS: ABIRATERONE ACETATE 125 mg/1 1

HIGHLIGHTS OF PRESCRIBING INFORMATION

Abiraterone Acetate. These highlights do not include all the information needed to use Abiraterone Acetate safely and effectively. See full prescribing information for Abiraterone Acetate.
Abiraterone Acetate tablets, for oral use
Initial U.S. Approval: 2011

1 INDICATIONS AND USAGE

Abiraterone Acetate is a CYP17 inhibitor indicated in combination with methylprednisolone for the treatment of patients with metastatic castration-resistant prostate cancer (CRPC). (1)

2 DOSAGE AND ADMINISTRATION

To avoid medication errors and overdose, be aware that Abiraterone Acetate tablets may have different dosing and food effects than other abiraterone acetate products.

Recommended dose: Abiraterone Acetate 500 mg (four 125 mg tablets) administered orally once daily in combination with methylprednisolone 4 mg administered orally twice daily. (2.1)

Patients receiving Abiraterone Acetate should also receive a gonadotropin-releasing hormone (GnRH) analog concurrently or should have had bilateral orchiectomy. (2.2)

Abiraterone Acetate tablets must be taken as a single dose once daily with or without food. The tablets should be swallowed whole with water. Do not crush or chew tablets. (2.1)

Dose Modification:

- For patients with baseline moderate hepatic impairment (Child-Pugh Class B), reduce the Abiraterone Acetate starting dose to 125 mg once daily. (2.3)
- For patients who develop hepatotoxicity during treatment, hold Abiraterone Acetate until recovery. Retreatment may be initiated at a reduced dose. Abiraterone Acetate should be discontinued if patients develop severe hepatotoxicity. (2.3)

3 DOSAGE FORMS AND STRENGTHS

Tablets: 125 mg (3)

4 CONTRAINDICATIONS

None

5 WARNINGS AND PRECAUTIONS

- Mineralocorticoid excess: Closely monitor patients with cardiovascular disease. Control hypertension and correct hypokalemia before treatment. Monitor blood pressure, serum potassium and symptoms of fluid retention at least monthly. (5.1)
- Adrenocortical insufficiency: Monitor for symptoms and signs of adrenocortical insufficiency. Increased dosage of corticosteroids may be indicated before, during and after stressful situations. (5.2)
- Hepatotoxicity: Can be severe and fatal. Monitor liver function and modify, interrupt, or discontinue Abiraterone Acetate as recommended. (5.3)
- Increased fractures and mortality in combination with radium Ra 223 dichloride: Use of Abiraterone Acetate plus methylprednisolone in combination with radium Ra 223 dichloride is not recommended. (5.4)
- Embryo-Fetal Toxicity: Abiraterone Acetate can cause fetal harm. Advise males with female partners of reproductive potential to use effective contraception. (5.5, 8.1, 8.3)
- Hypoglycemia: Severe hypoglycemia has been reported in patients with pre-existing diabetes who are taking medications containing thiazolidinediones (including pioglitazone) or repaglinide. Monitor blood glucose in patients with diabetes and assess if antidiabetic agent dose modifications are required. (5.6)

6 ADVERSE REACTIONS

The most common adverse reactions (≥ 10%) are fatigue, joint swelling or discomfort, edema, hot flush, diarrhea, vomiting, cough, hypertension, dyspnea, urinary tract infection and contusion. (6.1)

The most common laboratory abnormalities (> 20%) are anemia, elevated alkaline phosphatase, hypertriglyceridemia, lymphopenia, hypercholesterolemia, hyperglycemia, elevated AST, hypophosphatemia, elevated ALT and hypokalemia. (6.1)

To report SUSPECTED ADVERSE REACTIONS, contact Sun Pharmaceutical Industries, Inc. at 1-800-818-4555 or FDA at 1-800-FDA-1088 or www.FDA.gov/medwatch

7 DRUG INTERACTIONS

- CYP3A4 Inducers: Avoid concomitant strong CYP3A4 inducers during Abiraterone Acetate treatment. If a strong CYP3A4 inducer must be co-administered, increase the Abiraterone Acetate dosing frequency (2.4, 7.1)
- CYP2D6 Substrates: Avoid co-administration of Abiraterone Acetate with CYP2D6 substrates that have a narrow therapeutic index. If an alternative treatment cannot be used, exercise caution and consider a dose reduction of the concomitant CYP2D6 substrate (7.2)

8 USE IN SPECIFIC POPULATIONS

- Do not use Abiraterone Acetate in patients with baseline severe hepatic impairment (Child-Pugh Class C). (8.6)

FULL PRESCRIBING INFORMATION

1 INDICATIONS AND USAGE

Abiraterone Acetate is indicated in combination with methylprednisolone for the treatment of patients with metastatic castration-resistant prostate cancer.

2 DOSAGE AND ADMINISTRATION

2.1 Recommended Dosage

The recommended dose of Abiraterone Acetate is 500 mg (four 125 mg tablets) administered orally once daily in combination with methylprednisolone 4 mg administered orally twicedaily.

2.2 Important Administration Instructions

To avoid medication errors and overdose, be aware that abiraterone acetate tablets may have different dosing and food effects than other abiraterone acetate products. Patients receiving Abiraterone Acetate should also receive a gonadotropin-releasing hormone (GnRH) analog concurrently or should have had bilateral orchiectomy.

Abiraterone Acetate tablets must be taken as a single dose once daily with or without food [see Clinical Pharmacology (12.3)]. The tablets should be swallowed whole with water. Do not crush or chew tablets.

2.3 Dose Modification Guidelines in Hepatic Impairment and Hepatotoxicity

Hepatic Impairment

In patients with baseline moderate hepatic impairment (Child-Pugh Class B), reduce the recommended dose of Abiraterone Acetate to 125 mg once daily. In patients with moderate hepatic impairment monitor ALT, AST, and bilirubin prior to the start of treatment, every week for the first month, every two weeks for the following two months of treatment and monthly thereafter. If elevations in ALT and/or AST greater than 5X upper limit of normal (ULN) or total bilirubin greater than 3X ULN occur in patients with baseline moderate hepatic impairment, discontinue Abiraterone Acetate and do not re-treat patients with abiraterone acetate [see Use in Specific Populations (8.6) and Clinical Pharmacology (12.3)].

Do not use Abiraterone Acetate in patients with baseline severe hepatic impairment (Child-Pugh Class C).

Hepatotoxicity

For patients who develop hepatotoxicity during treatment with Abiraterone Acetate (ALT and/or AST greater than 5X ULN or total bilirubin greater than 3X ULN), interrupt treatment with Abiraterone Acetate [see Warnings and Precautions (5.3)]. Treatment may be restarted at a reduced dose of 375 mg once daily following return of liver function tests to the patient’s baseline or to AST and ALT less than or equal to 2.5X ULN and total bilirubin less than or equal to 1.5X ULN .For patients who resume treatment, monitor serum transaminases and bilirubin at a minimum of every two weeks for three months and monthly thereafter.

If hepatotoxicity recurs at the dose of 375 mg once daily, re-treatment may be restarted at a reduced dose of 250 mg once daily following return of liver function tests to the patient’s baseline or to AST and ALT less than or equal to 2.5X ULN and total bilirubin less than or equal to 1.5X ULN .

If hepatotoxicity recurs at the reduced dose of 250 mg once daily, discontinue treatment with Abiraterone Acetate.

Permanently discontinue Abiraterone Acetate for patients who develop a concurrent elevation of ALT greater than 3 x ULN and total bilirubin greater than 2 x ULN in the absence of biliary obstruction or other causes responsible for the concurrent elevation [see Warnings and Precautions (5.3)].

2.4 Dose Modification Guidelines for Strong CYP3A4 Inducers

Avoid concomitant strong CYP3A4 inducers (e.g., phenytoin, carbamazepine, rifampin, rifabutin, rifapentine, phenobarbital) during Abiraterone Acetate treatment.

If a strong CYP3A4 inducer must be co-administered, increase the Abiraterone Acetate dosing frequency to twice a day only during the co-administration period (e.g., from 500 mg once daily to 500 mg twice a day). Reduce the dose back to the previous dose and frequency, if the concomitant strong CYP3A4 inducer is discontinued [see Drug Interactions (7.1) and Clinical Pharmacology (12.3)].

3 DOSAGE FORMS AND STRENGTHS

Abiraterone acetate tablets, 125 mg, are white to off-white, oval-shaped tablets debossed with “125 FP” on one side.

4 CONTRAINDICATIONS

None.

5 WARNINGS AND PRECAUTIONS

5.1 Hypokalemia, Fluid Retention, and Cardiovascular Adverse Reactions due to Mineralocorticoid Excess

Abiraterone Acetate may cause hypertension, hypokalemia, and fluid retention as a consequence of increased mineralocorticoid levels resulting from CYP17 inhibition [see Clinical Pharmacology (12.1)]. Monitor patients for hypertension, hypokalemia, and fluid retention at least once a month. Control hypertension and correct hypokalemia before and during treatment with Abiraterone Acetate.

In the two randomized clinical trials, grade 3 to 4 hypertension occurred in 2% of patients, grade 3 to 4 hypokalemia in 4% of patients, and grade 3 to 4 edema in 1% of patients treated with abiraterone acetate [see Adverse Reactions (6)].

Closely monitor patients whose underlying medical conditions might be compromised by increases in blood pressure, hypokalemia or fluid retention, such as those with heart failure, recent myocardial infarction, cardiovascular disease, or ventricular arrhythmia. In postmarketing experience, QT prolongation and Torsades de Pointes have been observed in patients who develop hypokalemia while taking abiraterone acetate.

The safety of Abiraterone Acetate in patients with left ventricular ejection fraction < 50% or New York Heart Association (NYHA) Class III or IV heart failure (in Study 1) or NYHA Class II to IV heart failure (in Study 2) has not been established because these patients were excluded from these randomized clinical trials [see Clinical Studies (14)].

5.2 Adrenocortical Insufficiency

Adrenal insufficiency occurred in the two randomized clinical studies in 0.5% of patients taking abiraterone acetate and in 0.2% of patients taking placebo. Adrenocortical insufficiency was reported in patients receiving abiraterone acetate in combination with a corticosteroid, following interruption of daily steroids and/or with concurrent infection or stress.

Monitor patients for symptoms and signs of adrenocortical insufficiency, particularly if patients are withdrawn from corticosteroids, have corticosteroid dose reductions, or experience unusual stress. Symptoms and signs of adrenocortical insufficiency may be masked by adverse reactions associated with mineralocorticoid excess seen in patients treated with Abiraterone Acetate. If clinically indicated, perform appropriate tests to confirm the diagnosis of adrenocortical insufficiency. Increased dosage of corticosteroids may be indicated before, during and after stressful situations [see Warnings and Precautions (5.1)].

5.3 Hepatotoxicity

In postmarketing experience, there have been abiraterone acetate-associated severe hepatic toxicity, including fulminant hepatitis, acute liver failure and deaths [see Adverse Reactions (6.2)].

In the two randomized clinical trials, grade 3 or 4 ALT or AST increases (at least 5X ULN) were reported in 4% of patients who received abiraterone acetate, typically during the first 3 months after starting treatment. Patients whose baseline ALT or AST were elevated were more likely to experience liver test elevation than those beginning with normal values. Treatment discontinuation due to ALT and AST increases occurred in 1% of patients taking abiraterone acetate. In these clinical trials, no deaths clearly related to abiraterone acetate were reported due to hepatotoxicity events.

Measure serum transaminases (ALT and AST) and bilirubin levels prior to starting treatment with Abiraterone Acetate, every two weeks for the first three months of treatment and monthly thereafter. In patients with baseline moderate hepatic impairment receiving a reduced Abiraterone Acetate dose of 125 mg, measure ALT, AST, and bilirubin prior to the start of treatment, every week for the first month, every two weeks for the following two months of treatment and monthly thereafter. Promptly measure serum total bilirubin, AST, and ALT if clinical symptoms or signs suggestive of hepatotoxicity develop. Elevations of AST, ALT, or bilirubin from the patient's baseline should prompt more frequent monitoring. If at any time AST or ALT rise above five times the ULN, or the bilirubin rises above three times the ULN, interrupt Abiraterone Acetate treatment and closely monitor liver function.

Re-treatment with Abiraterone Acetate at a reduced dose level may take place only after return of liver function tests to the patient’s baseline or to AST and ALT less than or equal to 2.5X ULN and total bilirubin less than or equal to 1.5X ULN [see Dosage and Administration (2.3)].

Permanently discontinue treatment with Abiraterone Acetate for patients who develop a concurrent elevation of ALT greater than 3 x ULN and total bilirubin greater than 2 x ULN in the absence of biliary obstruction or other causes responsible for the concurrent elevation [see Dosage and Administration (2.3)].

The safety of Abiraterone Acetate re-treatment of patients who develop AST or ALT greater than or equal to 20X ULN and/or bilirubin greater than or equal to 10X ULN is unknown.

5.4 Increased Fractures and Mortality in Combination with Radium Ra 223 Dichloride

Abiraterone Acetate plus methylprednisolone is not recommended for use in combination with radium Ra 223 dichloride outside of clinical trials.

The clinical efficacy and safety of concurrent initiation of abiraterone acetate plus a corticosteroid and radium Ra 223 dichloride was assessed in a randomized, placebo-controlled multicenter study in 806 patients with asymptomatic or mildly symptomatic castration-resistant prostate cancer with bone metastases. The study was unblinded early based on an Independent Data Monitoring Committee recommendation.

At the primary analysis, increased incidences of fractures (28.6% vs 11.4%) and deaths (38.5% vs 35.5%) have been observed in patients who received abiraterone acetate plus a corticosteroid in combination with radium Ra 223 dichloride compared to patients who received placebo in combination with abiraterone acetate plus a corticosteroid.

5.5 Embryo-Fetal Toxicity

The safety and efficacy of Abiraterone Acetate have not been established in females. Based on animal reproductive studies and mechanism of action, Abiraterone Acetate can cause fetal harm and loss of pregnancy when administered to a pregnant female. In animal reproduction studies, oral administration of abiraterone acetate to pregnant rats during organogenesis caused adverse developmental effects at maternal exposures approximately ≥ 0.03 times the human exposure (AUC) at the recommended dose. Advise males with female partners of reproductive potential to use effective contraception during treatment with Abiraterone Acetate and for 3 weeks after the last dose of Abiraterone Acetate [see Use in Specific Populations (8.1,8.3)]. Abiraterone Acetate should not be handled by females who are or may become pregnant [see How Supplied/Storage and Handling (16)].

5.6 Hypoglycemia

Severe hypoglycemia has been reported when abiraterone acetate was administered to patients with pre-existing diabetes receiving medications containing thiazolidinediones (including pioglitazone) or repaglinide [see Drug Interactions (7.2)]. Monitor blood glucose in patients with diabetes during and after discontinuation of treatment with Abiraterone Acetate. Assess if antidiabetic drug dosage needs to be adjusted to minimize the risk of hypoglycemia.

6 ADVERSE REACTIONS

The following are discussed in more detail in other sections of the labeling:

- Hypokalemia, Fluid Retention, and Cardiovascular Adverse Reactions due to Mineralocorticoid Excess [see Warnings and Precautions (5.1)].
- Adrenocortical Insufficiency [see Warnings and Precautions (5.2)].
- Hepatotoxicity [see Warnings and Precautions (5.3)].
- Increased Fractures and Mortality in Combination with Radium Ra 223 Dichloride [see Warnings and Precautions (5.4)].

6.1 Clinical Trial Experience

Because clinical trials are conducted under widely varying conditions, adverse reaction rates observed in the clinical trials of a drug cannot be directly compared to rates in the clinical trials of another drug and may not reflect the rates observed in clinical practice.

Two randomized placebo-controlled, multicenter clinical trials (Study 1 and Study 2) enrolled patients who had metastatic castration-resistant prostate cancer who were using a gonadotropin-releasing hormone (GnRH) agonist or were previously treated with orchiectomy. In both Study 1 and Study 2 abiraterone acetate was administered at a dose equivalent to 500 mg of Abiraterone Acetate daily in combination with a different corticosteroid twice daily in the active treatment arms. Placebo plus corticosteroid was given to control patients.

The most common adverse drug reactions (>10%) reported in the two randomized clinical trials that occurred more commonly (>2%) in the abiraterone acetate arm were fatigue, joint swelling or discomfort, edema, hot flush, diarrhea, vomiting, cough, hypertension, dyspnea, urinary tract infection and contusion.

The most common laboratory abnormalities (>20%) reported in the two randomized clinical trials that occurred more commonly (≥2%) in the abiraterone acetate arm were anemia, elevated alkaline phosphatase, hypertriglyceridemia, lymphopenia, hypercholesterolemia, hyperglycemia, elevated AST, hypophosphatemia, elevated ALT and hypokalemia.

Study 1: Metastatic CRPC Following Chemotherapy

Study 1 enrolled 1195 patients with metastatic CRPC who had received prior docetaxel chemotherapy. Patients were not eligible if AST and/or ALT ≥ 2.5X ULN in the absence of liver metastases. Patients with liver metastases were excluded if AST and/or ALT > 5X ULN.

Table 1 shows adverse reactions on the abiraterone acetate arm in Study 1 that occurred with a ≥2% absolute increase in frequency compared to placebo or were events of special interest. The median duration of treatment with abiraterone acetate with a corticosteroid was 8 months.

Table 1: Adverse Reactions due to Abiraterone Acetate in Study 1

 | Abiraterone Acetate with Corticosteroid(N=791) |  | Placebo with Corticosteroid (N=394)
System Organ Class; Adverse Reaction | All Grades1; % | Grade 3-4; % | All Grades; % | Grade 3-4; %
Musculoskeletal and connective tissue disorders
Joint swelling/ discomfort2 | 30 | 4.2 | 23 | 4.1
Muscle discomfort3 | 26 | 3.0 | 23 | 2.3
General Disorders
Edema4 | 27 | 1.9 | 18 | 0.8
Vascular Disorders
Hot Flush | 19 | 0.3 | 17 | 0.3
Hypertension | 8.5 | 1.3 | 6.9 | 0.3
Gastrointestinal Disorders
Diarrhea | 18 | 0.6 | 14 | 1.3
Dyspepsia | 6.1 | 0 | 3.3 | 0
Infections and infestations
Urinary tract infection | 12 | 2.1 | 7.1 | 0.5
Upper respiratory tract infection | 5.4 | 0 | 2.5 | 0
Respiratory, thoracic and mediastinal disorders
Cough | 11 | 0 | 7.6 | 0
Renal and urinary disorders
Urinary frequency | 7.2 | 0.3 | 5.1 | 0.3
Nocturia | 6.2 | 0 | 4.1 | 0
Injury, poisoning and procedural complications
Fractures5 | 5.9 | 1.4 | 2.3 | 0
Cardiac disorders
Arrhythmia6 | 7.2 | 1.1 | 4.6 | 1.0
Chest pain or chest discomfort7 | 3.8 | 0.5 | 2.8 | 0
Cardiac failure8 | 2.3 | 1.9 | 1.0 | 0.3
1 Adverse events graded according to CTCAE version 3.0
2 Includes terms Arthritis, Arthralgia, Joint swelling, and Joint stiffness
3 Includes terms Muscle spasms, Musculoskeletal pain, Myalgia, Musculoskeletal discomfort, and Musculoskeletal stiffness
4 Includes terms Edema, Edema peripheral, Pitting edema, and Generalized edema
5 Includes all fractures with the exception of pathological fracture
6 Includes terms Arrhythmia, Tachycardia, Atrial fibrillation, Supraventricular tachycardia, Atrial tachycardia, Ventricular tachycardia, Atrial flutter, Bradycardia, Atrioventricular block complete, Conduction disorder, and Bradyarrhythmia
7 Includes terms Angina pectoris, Chest pain, and Angina unstable. Myocardial infarction or ischemia occurred more commonly in the placebo arm than in the abiraterone acetate arm (1.3% vs. 1.1% respectively).
8 Includes terms Cardiac failure, Cardiac failure congestive, Left ventricular dysfunction, Cardiogenic shock, Cardiomegaly, Cardiomyopathy, and Ejection fraction decreased

Table 2 shows laboratory abnormalities of interest from Study 1. Grade 3-4 low serum phosphorus (7%) and low potassium (5%) occurred at a greater than or equal to 5% rate in the abiraterone acetate with a corticosteroid arm.

Table 2: Laboratory Abnormalities of Interest in Study 1

 | Abiraterone Acetate with Corticosteroid(N=791) |  | Placebo with Corticosteroid(N=394)
Laboratory Abnormality | All Grades; % | Grade 3-4; % | All Grades; % | Grade 3-4; %
Hypertriglyceridemia | 63 | 0.4 | 53 | 0
High AST | 31 | 2.1 | 36 | 1.5
Hypokalemia | 28 | 5.3 | 20 | 1.0
Hypophosphatemia | 24 | 7.2 | 16 | 5.8
High ALT | 11 | 1.4 | 10 | 0.8
High Total Bilirubin | 6.6 | 0.1 | 4.6 | 0

Study 2: Metastatic CRPC Prior to Chemotherapy

Study 2 enrolled 1088 patients with metastatic CRPC who had not received prior cytotoxic chemotherapy. Patients were ineligible if AST and/or ALT ≥ 2.5X ULN and patients were excluded if they had liver metastases.

Table 3 shows adverse reactions on the abiraterone acetate arm in Study 2 that occurred in ≥ 5% of patients with a ≥ 2% absolute increase in frequency compared to placebo. The median duration of treatment with abiraterone acetate with a corticosteroid was 13.8 months.

Table 3: Adverse Reactions in ≥5% of Patients on the Abiraterone Acetate Arm in Study 2

 | Abiraterone Acetate with Corticosteroid(N=542) |  | Placebo with Corticosteroid(N=540)
System Organ Class; Adverse Reaction | All Grades1; % | Grade 3-4; % | All Grades; % | Grade 3-4; %
General Disorders
Fatigue | 39 | 2.2 | 34 | 1.7
Edema2 | 25 | 0.4 | 21 | 1.1
Pyrexia | 8.7 | 0.6 | 5.9 | 0.2
Musculoskeletal and connective tissue disorders
Joint swelling/ discomfort3 | 30 | 2.0 | 25 | 2.0
Groin Pain | 6.6 | 0.4 | 4.1 | 0.7
Gastrointestinal Disorders
Constipation | 23 | 0.4 | 19 | 0.6
Diarrhea | 22 | 0.9 | 18 | 0.9
Dyspepsia | 11 | 0.0 | 5.0 | 0.2
Vascular Disorders
Hot Flush | 22 | 0.2 | 18 | 0.0
Hypertension | 22 | 3.9 | 13 | 3.0
Respiratory, thoracic and mediastinal disorders
Cough | 17 | 0.0 | 14 | 0.2
Dyspnea | 12 | 2.4 | 9.6 | 0.9
Psychiatric Disorders
Insomnia | 14 | 0.2 | 11 | 0.0
Injury, poisoning and procedural complications
Contusion | 13 | 0.0 | 9.1 | 0.0
Falls | 5.9 | 0.0 | 3.3 | 0.0
Infections and infestations
Upper respiratory tract infection | 13 | 0.0 | 8.0 | 0.0
Nasopharyngitis | 11 | 0.0 | 8.1 | 0.0
Renal and urinary disorders
Hematuria | 10 | 1.3 | 5.6 | 0.6
Skin and subcutaneous tissue disorders
Rash | 8.1 | 0.0 | 3.7 | 0.0
1 Adverse events graded according to CTCAE version 3.0
2 Includes terms Edema peripheral, Pitting edema, and Generalized edema
3 Includes terms Arthritis, Arthralgia, Joint swelling, and Joint stiffness

Table 4 shows laboratory abnormalities that occurred in greater than 15% of patients, and more frequently (>5%) in the abiraterone acetate arm compared to placebo in Study 2.

Table 4: Laboratory Abnormalities in > 15% of Patients in the Abiraterone Acetate Arm of Study 2

 | Abiraterone Acetate with Corticosteroid(N=542) |  | Placebo with Corticosteroid(N=540)
Laboratory Abnormality | Grade 1-4; % | Grade 3-4; % | Grade 1-4; % | Grade 3-4; %
Hematology
Lymphopenia | 38 | 8.7 | 32 | 7.4
Chemistry
Hyperglycemia1 | 57 | 6.5 | 51 | 5.2
High ALT | 42 | 6.1 | 29 | 0.7
High AST | 37 | 3.1 | 29 | 1.1
Hypernatremia | 33 | 0.4 | 25 | 0.2
Hypokalemia | 17 | 2.8 | 10 | 1.7
1 Based on non-fasting blood draws

Cardiovascular Adverse Reactions

In the combined data for studies 1 and 2, cardiac failure occurred more commonly in patients treated with abiraterone acetate compared to patients on the placebo arm (2.1% versus 0.7%). Grade 3-4 cardiac failure occurred in 1.6% of patients taking abiraterone acetate and led to 5 treatment discontinuations and 2 deaths. Grade 3-4 cardiac failure occurred in 0.2% of patients taking placebo. There were no treatment discontinuations and one death due to cardiac failure in the placebo group.

In Study 1 and 2, the majority of arrhythmias were grade 1 or 2. There was one death associated with arrhythmia and one patient with sudden death in the abiraterone acetate arms and no deaths in the placebo arms. There were 7 (0.5 %) deaths due to cardiorespiratory arrest in the abiraterone acetate arms and 3 (0.3 %) deaths in the placebo arms. Myocardial ischemia or myocardial infarction led to death in 3 patients in the placebo arms and 2 deaths in the abiraterone acetate arms.

6.2 Postmarketing Experience

The following additional adverse reactions have been identified during post approval use of abiraterone acetate with a different corticosteroid. Because these reactions are reported voluntarily from a population of uncertain size, it is not always possible to reliably estimate their frequency or establish a causal relationship to drug exposure.

Respiratory, Thoracic and Mediastinal Disorders:non-infectious pneumonitis.

Musculoskeletal and Connective Tissue Disorders:myopathy, including rhabdomyolysis.

Hepatobiliary Disorders:fulminant hepatitis, including acute hepatic failure and death.

Cardiac Disorders:QT prolongation and Torsades de Pointes (observed in patients who developed hypokalemia or had underlying cardiovascular conditions).

Immune System Disorders – Hypersensitivity:anaphylactic reactions (severe allergic reactions that include, but are not limited to difficulty swallowing or breathing, swollen face, lips, tongue or throat, or an itchy rash (urticaria)).

7 DRUG INTERACTIONS

7.1 Effect of Other Drugs on Abiraterone Acetate

Strong CYP3A4 Inducers

The co-administration of rifampin, a strong CYP3A4 inducer, decreased exposure of abiraterone by 55%. Avoid concomitant strong CYP3A4 inducers during Abiraterone Acetate treatment. If a strong CYP3A4 inducer must be co-administered with Abiraterone Acetate, increase the Abiraterone Acetate dosing frequency [see Dosage and Administration (2.4) and Clinical Pharmacology (12.3)].

7.2 Effect of Abiraterone Acetate on Other Drugs

CYP2D6 Substrates

Abiraterone is an inhibitor of the hepatic drug-metabolizing enzymes CYP2D6. The co-administration of Abiraterone Acetate with CYP2D6 substrates increases the concentration of the CYP2D6 substrate, which may increase the frequency and/or severity of adverse reactions of these substrates. Avoid co-administration of abiraterone acetate with substrates of CYP2D6 with a narrow therapeutic index. If alternative treatments cannot be used, consider a dose reduction of the concomitant CYP2D6 substrate drug in accordance with its Prescribing Information [see Clinical Pharmacology (12.3)].

CYP2C8 Substrates

Abiraterone is an inhibitor of the hepatic drug-metabolizing enzymes CYP2D6 and CYP2C8. The co-administration of Abiraterone Acetate with CYP2C8 substrates increases the concentration of the CYP2C8 substrate, which may increase the frequency and/or severity of adverse reactions of these substrates. Therefore, patients should be monitored closely for signs of toxicity related to a CYP2C8 substrate with a narrow therapeutic index if used concomitantly with abiraterone acetate [see Clinical Pharmacology (12.3)].

8 USE IN SPECIFIC POPULATIONS

8.1 Pregnancy

Risk Summary

The safety and efficacy of Abiraterone Acetate have not been established in females. Based on findings from animal studies and the mechanism of action, Abiraterone Acetate can cause fetal harm and potential loss of pregnancy.

There are no human data on the use of Abiraterone Acetate in pregnant women. In animal reproduction studies, oral administration of abiraterone acetate to pregnant rats during organogenesis, caused adverse developmental effects at maternal exposures of approximately ≥ 0.03 times the human exposure (AUC) at the recommended dose (see Data).

Data

Animal Data

In an embryo-fetal developmental toxicity study in rats, abiraterone acetate caused developmental toxicity when administered at oral doses of 10, 30 or 100 mg/kg/day throughout the period of organogenesis (gestational days 6-17). Findings included embryo-fetal lethality (increased post implantation loss and resorptions and decreased number of live fetuses), fetal developmental delay (skeletal effects) and urogenital effects (bilateral ureter dilation) at doses >10 mg/kg/day, decreased fetal ano-genital distance at >30 mg/kg/day, and decreased fetal body weight at 100 mg/kg/day. Doses >10 mg/kg/day caused maternal toxicity. The doses tested in rats resulted in systemic exposures (AUC) approximately 0.03, 0.1 and 0.3 times, respectively, the AUC in patients.

8.2 Lactation

Risk Summary

The safety and efficacy of Abiraterone Acetate have not been established in females. There is no information available on the presence of abiraterone acetate in human milk, or on the effects on the breastfed child or milk production.

8.3 Females and Males of Reproductive Potential

Contraception

Males

Based on findings in animal reproduction studies and its mechanism of action, advise male patients with female partners of reproductive potential to use effective contraception during treatment and for 3 weeks after the last dose of Abiraterone Acetate [see Use in Specific Populations (8.1)].

Infertility

Based on animal studies, abiraterone acetate may impair reproductive function and fertility in males of reproductive potential [see Nonclinical Toxicology (13.1)].

8.4 Pediatric Use

Safety and effectiveness of abiraterone acetate in pediatric patients have not been established.

8.5 Geriatric Use

Of the total number of patients receiving abiraterone acetate in the two randomized trials, 73% of patients were 65 years and over and 30% were 75 years and over. No overall differences in safety or effectiveness were observed between these elderly patients and younger patients. Other reported clinical experience has not identified differences in responses between the elderly and younger patients, but greater sensitivity of some older individuals cannot be ruled out.

8.6 Hepatic Impairment

The pharmacokinetics of abiraterone were examined in subjects with baseline mild (N=8) or moderate (N=8) hepatic impairment (Child-Pugh Class A and B, respectively) and in 8 healthy control subjects with normal hepatic function. The systemic exposure (AUC) of abiraterone after a single oral dose equivalent to 500 mg of Abiraterone Acetate increased by approximately 1.1-fold and 3.6-fold in subjects with mild and moderate baseline hepatic impairment, respectively compared to subjects with normal hepatic function.

In another trial, the pharmacokinetics of abiraterone were examined in subjects with baseline severe (N=8) hepatic impairment (Child-Pugh Class C) and in 8 healthy control subjects with normal hepatic function. The systemic exposure (AUC) of abiraterone increased by approximately 7-fold and the fraction of free drug increased 2-fold in subjects with severe baseline hepatic impairment compared to subjects with normal hepatic function.

No dosage modification is recommended for patients with baseline mild hepatic impairment (Child-Pugh Class A). In patients with baseline moderate hepatic impairment (Child-Pugh Class B), reduce the recommended dose of Abiraterone Acetate to 125 mg once daily. Do not use in patients with baseline severe hepatic impairment (Child-Pugh Class C). If elevations in ALT or AST >5X ULN or total bilirubin >3X ULN occur in patients with baseline moderate hepatic impairment, discontinue abiraterone acetate treatment [see Dosage and Administration (2.3) and Clinical Pharmacology (12.3)].

For patients who develop hepatotoxicity during treatment, interruption of treatment and dosage adjustment may be required [see Dosage and Administration (2.3), Warnings and Precautions (5.3), and Clinical Pharmacology (12.3)].

8.7 Renal Impairment

No dosage modification is recommended for patients with renal impairment [see Clinical Pharmacology (12.3)].

10 OVERDOSAGE

Human experience of overdose with Abiraterone Acetate is limited.

There is no specific antidote. In the event of an overdose, stop Abiraterone Acetate, undertake general supportive measures, including monitoring for arrhythmias and cardiac failure and assess liver function.

11 DESCRIPTION

Abiraterone acetate, the active ingredient of Abiraterone Acetate tablet is the acetyl ester of abiraterone. Abiraterone is an inhibitor of CYP17 (17α-hydroxylase/C17,20-lyase). Each Abiraterone Acetate Tablet contains 125 mg of abiraterone acetate. Abiraterone acetate is designated chemically as (3β)-17-(3-pyridinyl) androsta-5,16-dien-3-yl acetate and its structure is:

Abiraterone acetate is micronized (smaller particle size) white to off-white, non-hygroscopic, crystalline powder. Its molecular formula is C26H33NO2and it has a molecular weight of 391.55. Abiraterone acetate is a lipophilic compound with an octanol-water partition coefficient of 5.12 (Log P) and is practically insoluble in water. The pKa of the aromatic nitrogen is 5.19.

Inactive ingredients in the tablets are lactose monohydrate, microcrystalline cellulose, croscarmellose sodium, sodium lauryl sulfate, sodium stearyl fumarate, butylated hydroxyanisole, butylated hydroxytoluene.

12 CLINICAL PHARMACOLOGY

12.1 Mechanism of Action

Abiraterone acetate is converted in vivoto abiraterone, an androgen biosynthesis inhibitor, that inhibits 17 α-hydroxylase/C17,20-lyase (CYP17). This enzyme is expressed in testicular, adrenal, and prostatic tumor tissues and is required for androgen biosynthesis.

CYP17 catalyzes two sequential reactions: 1) the conversion of pregnenolone and progesterone to their 17α-hydroxy derivatives by 17α-hydroxylase activity and 2) the subsequent formation of dehydroepiandrosterone (DHEA) and androstenedione, respectively, by C17,20-lyase activity. DHEA and androstenedione are androgens and are precursors of testosterone. Inhibition of CYP17 by abiraterone can also result in increased mineralocorticoid production by the adrenals [see Warnings and Precautions (5.1)].

Androgen sensitive prostatic carcinoma responds to treatment that decreases androgen levels. Androgen deprivation therapies, such as treatment with GnRH agonists or orchiectomy, decrease androgen production in the testes but do not affect androgen production by the adrenals or in the tumor.

Abiraterone acetate decreased serum testosterone and other androgens in patients in the placebo-controlled clinical trial. It is not necessary to monitor the effect of Abiraterone Acetate on serum testosterone levels.

Changes in serum prostate specific antigen (PSA) levels may be observed but have not been shown to correlate with clinical benefit in individual patients.

12.2 Pharmacodynamics

In a clinical study in patients with metastatic CRPC who were treated with Abiraterone Acetate 500 mg once daily and methylprednisolone 4 mg twice daily for 84 days, the average serum testosterone level ± standard deviation (SD) on days 9 and 10 of treatment was 0.33 ± 0.09 ng/dL.

Cardiac Electrophysiology

In a multi-center, open-label, single-arm trial, 33 patients with metastatic CRPC received a dose of 1,000 mg once daily orally of another abiraterone acetate product at least 1 hour before or 2 hours after a meal in combination with a different corticosteroid orally twice daily. Assessments up to Cycle 2 Day 2 showed no large changes in the QTc interval (i.e., >20 ms) from baseline. However, small increases in the QTc interval (i.e., <10 ms) due to abiraterone acetate cannot be excluded due to study design limitations.

12.3 Pharmacokinetics

Following administration of abiraterone acetate, the pharmacokinetics of abiraterone have been studied in healthy subjects and in patients with metastatic CRPC. In vivo, abiraterone acetate is converted to abiraterone. In clinical studies of other abiraterone acetate formulations, abiraterone acetate plasma concentrations were below detectable levels (< 0.2 ng/mL) in > 99% of the analyzed samples.

Geometric mean ±SD abiraterone Cmaxwas 73 ± 44 ng/mL and AUC0-∞was 373 ± 249 ng·hr/mL following a single dose of Abiraterone Acetate 500 mg in overnight fasted healthy subjects. Dose proportionality was observed in single doses of Abiraterone Acetate in a range of 125 mg to 625 mg.

Absorption

Following oral administration of Abiraterone Acetate to patients with metastatic CRPC, the median time to reach maximum plasma abiraterone concentrations is 2 hours.

Effect of Food

Abiraterone Cmaxwas approximately 6.5-fold higher and AUC0-∞was 4.4-fold higher when a single dose of Abiraterone Acetate 500 mg was administered with a high-fat meal (56-60% fat, 900-1,000 calories) compared to overnight fasting in healthy subjects.

Abiraterone Acetate can be taken with or without food.

Distribution

Abiraterone is highly bound (>99%) to the human plasma proteins, albumin and alpha-1 acid glycoprotein. The apparent steady-state volume of distribution (mean ± SD) is 19,669 ± 13,358 L.

Elimination

In patients with metastatic CRPC, the mean terminal half-life of abiraterone in plasma (mean ± SD) is 12 ± 5 hours.

Metabolism

Following oral administration of^14C-abiraterone acetate as capsules, abiraterone acetate is hydrolyzed to abiraterone (active metabolite). The conversion is likely through esterase activity (the esterases have not been identified) and is not CYP mediated. The two main circulating metabolites of abiraterone in human plasma are abiraterone sulphate (inactive) and N-oxide abiraterone sulphate (inactive), which account for about 43% of exposure each. CYP3A4 and SULT2A1 are the enzymes involved in the formation of N-oxide abiraterone sulphate and SULT2A1 is involved in the formation of abiraterone sulphate.

Excretion

Following oral administration of^14C-abiraterone acetate, approximately 88% of the radioactive dose is recovered in feces and approximately 5% in urine. The major compounds present in feces are unchanged abiraterone acetate and abiraterone (approximately 55% and 22% of the administered dose, respectively).

Specific Populations

Patients with Hepatic Impairment

The pharmacokinetics of abiraterone was examined in subjects with baseline mild (N=8) or moderate (N=8) hepatic impairment (Child-Pugh Class A and B, respectively) and in 8 healthy control subjects with normal hepatic function. Systemic exposure to abiraterone after a single oral 1,000 mg dose of another abiraterone acetate product given under fasting conditions increased approximately 1.1-fold and 3.6-fold in subjects with mild and moderate baseline hepatic impairment, respectively. The mean half-life of abiraterone is prolonged to approximately 18 hours in subjects with mild hepatic impairment and to approximately 19 hours in subjects with moderate hepatic impairment.

In another trial, the pharmacokinetics of abiraterone were examined in subjects with baseline severe (N=8) hepatic impairment (Child-Pugh Class C) and in 8 healthy control subjects with normal hepatic function. The systemic exposure (AUC) of abiraterone increased by approximately 7-fold in subjects with severe baseline hepatic impairment compared to subjects with normal hepatic function. In addition, the mean protein binding was found to be lower in the severe hepatic impairment group compared to the normal hepatic function group, which resulted in a two-fold increase in the fraction of free drug in patients with severe hepatic impairment.

Patients with Renal Impairment

The pharmacokinetics of abiraterone were examined in patients with end-stage renal disease (ESRD) on a stable hemodialysis schedule (N=8) and in matched control subjects with normal renal function (N=8). In the ESRD cohort of the trial, a single 1,000 mg dose of another abiraterone acetate product was given under fasting conditions 1 hour after dialysis, and samples for pharmacokinetic analysis were collected up to 96 hours post dose. Systemic exposure to abiraterone after a single oral 1,000 mg dose of another abiraterone acetate product did not increase in subjects with end-stage renal disease on dialysis, compared to subjects with normal renal function.

Drug Interactions Studies

Clinical Studies

Effect of Other Drugs on Abiraterone

Strong CYP3A4 inducers:In a clinical pharmacokinetic interaction study of healthy subjects, pretreated with a strong CYP3A4 inducer (rifampin, 600 mg daily for 6 days) followed by a single dose of 1,000 mg of another abiraterone acetate product that is dose equivalent to a single Abiraterone Acetate 500 mg dose, the mean plasma AUC∞of abiraterone was decreased by 55%.

Strong CYP3A4 inhibitors:Co-administration of ketoconazole, a strong inhibitor of CYP3A4, had no clinically meaningful effect on the pharmacokinetics of abiraterone.

Effect of Abiraterone on Other Drugs

CYP2D6 substrates:The Cmaxand AUC of dextromethorphan (CYP2D6 substrate) were increased 2.8- and 2.9-fold, respectively when dextromethorphan 30 mg was given with another abiraterone acetate product of 1,000 mg daily that is dose equivalent to Abiraterone Acetate 500 mg daily. The AUC for dextrorphan, the active metabolite of dextromethorphan, increased approximately 1.3 fold.

CYP1A2 substrates:When another abiraterone acetate product of 1,000 mg daily that is dose equivalent to Abiraterone Acetate 500 mg daily was given with a single dose of 100 mg theophylline (CYP1A2 substrate), no increase in systemic exposure of theophylline was observed.

CYP2C8 substrates:The AUC of pioglitazone (CYP2C8 substrate) was increased by 46% when pioglitazone was given to healthy subjects with a single dose of 1,000 mg of another abiraterone acetate product that is dose equivalent to a single Abiraterone Acetate 500 mg dose .

In Vitro Studies

Cytochrome P450 (CYP) Enzymes:Abiraterone is a substrate of CYP3A4 and has the potential to inhibit CYP1A2, CYP2D6, CYP2C8 and to a lesser extent CYP2C9, CYP2C19 and CYP3A4/5.

Transporter Systems:In vitro studies show that at clinically relevant concentrations, abiraterone acetate and abiraterone are not substrates of P-glycoprotein (P-gp) and that abiraterone acetate is an inhibitor of P-gp. In vitro, abiraterone and its major metabolites were shown to inhibit the hepatic uptake transporter OATP1B1. There are no clinical data available to confirm transporter based interaction.

13 NONCLINICAL TOXICOLOGY

13.1 Carcinogenesis, Mutagenesis, and Impairment of Fertility

A two-year carcinogenicity study was conducted in rats at abiraterone acetate oral doses of 5, 15, and 50 mg/kg/day for males and 15, 50, and 150 mg/kg/day for females. Abiraterone acetate increased the combined incidence of interstitial cell adenomas and carcinomas in the testes at all dose levels tested. This finding is considered to be related to the pharmacological activity of abiraterone. Rats are regarded as more sensitive than humans to developing interstitial cell tumors in the testes. Abiraterone acetate was not carcinogenic in female rats at exposure levels up to 0.8 times the human clinical exposure based on AUC. Abiraterone acetate was not carcinogenic in a 6-month study in the transgenic (Tg.rasH2) mouse.

Abiraterone acetate and abiraterone was not mutagenic in an in vitromicrobial mutagenesis (Ames) assay or clastogenic in an in vitrocytogenetic assay using primary human lymphocytes or an in vivorat micronucleus assay.

In repeat-dose toxicity studies in male rats (13- and 26-weeks) and monkeys (39-weeks), atrophy, aspermia/hypospermia, and hyperplasia in the reproductive system were observed at ≥ 50 mg/kg/day in rats and ≥ 250 mg/kg/day in monkeys and were consistent with the antiandrogenic pharmacological activity of abiraterone. These effects were observed in rats at systemic exposures similar to humans and in monkeys at exposures approximately 0.6 times the AUC in humans.

In a fertility study in male rats, reduced organ weights of the reproductive system, sperm counts, sperm motility, altered sperm morphology and decreased fertility were observed in animals dosed for 4 weeks at ≥ 30 mg/kg/day orally. Mating of untreated females with males that received 30 mg/kg/day oral abiraterone acetate resulted in a reduced number of corpora lutea, implantations and live embryos and an increased incidence of pre-implantation loss. Effects on male rats were reversible after 16 weeks from the last abiraterone acetate administration.

In a fertility study in female rats, animals dosed orally for 2 weeks until day 7 of pregnancy at >30 mg/kg/day had an increased incidence of irregular or extended estrous cycles and pre-implantation loss (300 mg/kg/day). There were no differences in mating, fertility, and litter parameters in female rats that received abiraterone acetate. Effects on female rats were reversible after 4 weeks from the last abiraterone acetate administration.

The dose of 30 mg/kg/day in rats is approximately 0.6 times the recommended dose of 500 mg of Abiraterone Acetate/day based on body surface area.

In 13- and 26-week studies in rats and 13- and 39-week studies in monkeys, a reduction in circulating testosterone levels occurred with abiraterone acetate at approximately one half the human clinical exposure based on AUC. As a result, decreases in organ weights and toxicities were observed in the male and female reproductive system, adrenal glands, liver, pituitary (rats only), and male mammary glands. The changes in the reproductive organs are consistent with the antiandrogenic pharmacological activity of abiraterone acetate.

13.2 Animal Toxicology and/or Pharmacology

A dose-dependent increase in cataracts was observed in rats after daily oral abiraterone acetate administration for 26 weeks starting at ≥ 50 mg/kg/day (similar to the human clinical exposure based on AUC). In a 39-week monkey study with daily oral abiraterone acetate administration, no cataracts were observed at higher doses (2 times greater than the clinical exposure based on AUC).

14 CLINICAL STUDIES

The efficacy and safety of abiraterone acetate with prednisone in patients with metastatic castration-resistant prostate cancer (CRPC) that has progressed on androgen deprivation therapy was demonstrated in two randomized, placebo-controlled, international clinical studies. Patients with prior ketoconazole treatment for prostate cancer and a history of adrenal gland or pituitary disorders were excluded from these trials. Concurrent use of spironolactone was not allowed during the study period.

Study 1: Patients with metastatic CRPC who had received prior docetaxel chemotherapy

A total of 1195 patients were randomized 2:1 to receive either abiraterone acetate orally at a dose equivalent to 500 mg of Abiraterone Acetate once daily in combination with a different corticosteroid orally twice daily (N=797) or placebo once daily plus a different corticosteroid orally twice daily (N=398). Patients randomized to either arm were to continue treatment until disease progression (defined as a 25% increase in PSA over the patient’s baseline/nadir together with protocol-defined radiographic progression and symptomatic or clinical progression), initiation of new treatment, unacceptable toxicity or withdrawal.

The following patient demographics and baseline disease characteristics were balanced between the treatment arms. The median age was 69 years (range 39-95) and the racial distribution was 93% Caucasian, 3.6% Black, 1.7% Asian, and 1.6% Other. Eighty-nine percent of patients enrolled had an ECOG performance status score of 0-1 and 45% had a Brief Pain Inventory-Short Form score of ≥ 4 (patient’s reported worst pain over the previous 24 hours). Ninety percent of patients had metastases in bone and 30% had visceral involvement. Seventy percent of patients had radiographic evidence of disease progression and 30% had PSA-only progression. Seventy percent of patients had previously received one cytotoxic chemotherapy regimen and 30% received two regimens.

The protocol pre-specified interim analysis was conducted after 552 deaths and showed a statistically significant improvement in overall survival (OS) in patients treated with abiraterone acetate with a corticosteroid compared to patients in the placebo with a corticosteroid arm (Table 5and Figure 1). An updated survival analysis was conducted when 775 deaths (97% of the planned number of deaths for final analysis) were observed. Results from this analysis were consistent with those from the interim analysis (Table 5).

Table 5: Overall Survival of Patients Treated with Either Abiraterone Acetate or Placebo in Combination with Corticosteroid in Study 1 (Intent-to-Treat Analysis)

 | Abiraterone Acetate with Corticosteroid(N=797) | Placebo with Corticosteroid(N=398)
Primary Survival Analysis
Deaths (%) | 333 (42%) | 219 (55%)
Median survival (months) | 14.8 (14.1, 15.4) | 10.9 (10.2, 12.0)
(95% CI); p-value1 |  | <0.0001
Hazard ratio (95% CI)2 |  | 0.646 (0.543, 0.768)
Updated Survival Analysis
Deaths (%) | 501 (63%) | 274 (69%)
Median survival (months) | 15.8 (14.8, 17.0) | 11.2 (10.4, 13.1)
(95% CI)
Hazard ratio (95% CI)2 |  | 0.740 (0.638, 0.859)
1 p-value is derived from a log-rank test stratified by ECOG performance status score (0-1 vs. 2), pain score (absent vs. present), number of prior chemotherapy regimens (1 vs. 2), and type of disease progression (PSA only vs. radiographic)
2 Hazard Ratio is derived from a stratified proportional hazards model. Hazard ratio <1 favors abiraterone acetate with prednisone.

Figure 1: Kaplan-Meier Overall Survival Curves in Study 1 (Intent-to-Treat Analysis)

Study 2: Patients with metastatic CRPC who had not received prior cytotoxic chemotherapy

In Study 2, 1088 patients were randomized 1:1 to receive either abiraterone acetate at a dose equivalent to 500 mg of Abiraterone Acetate once daily (N=546) or Placebo orally once daily (N=542). Both arms were also given a different corticosteroid twice daily. Patients continued treatment until radiographic or clinical (cytotoxic chemotherapy, radiation or surgical treatment for cancer, pain requiring chronic opioids, or ECOG performance status decline to 3 or more) disease progression, unacceptable toxicity or withdrawal. Patients with moderate or severe pain, opiate use for cancer pain, or visceral organ metastases were excluded.

Patient demographics were balanced between the treatment arms. The median age was 70 years. The racial distribution of patients treated with abiraterone acetate was 95% Caucasian, 2.8% Black, 0.7% Asian and 1.1% Other. The ECOG performance status was 0 for 76% of patients, and 1 for 24% of patients. Co-primary efficacy endpoints were overall survival and radiographic progression-free survival (rPFS). Baseline pain assessment was 0-1 (asymptomatic) in 66% of patients and 2-3 (mildly symptomatic) in 26% of patients as defined by the Brief Pain Inventory-Short Form (worst pain over the last 24 hours).

Radiographic progression-free survival was assessed with the use of sequential imaging studies and was defined by bone scan identification of 2 or more new bone lesions with confirmation (Prostate Cancer Working Group 2 criteria) and/or modified Response Evaluation Criteria In Solid Tumors (RECIST) criteria for progression of soft tissue lesions. Analysis of rPFS utilized centrally-reviewed radiographic assessment of progression.

The planned final analysis for OS, conducted after 741 deaths (median follow up of 49 months) demonstrated a statistically significant OS improvement in patients treated with abiraterone acetate with a corticosteroid compared to those treated with placebo with a corticosteroid (Table 6and Figure 2). Sixty-five percent of patients on the abiraterone acetate arm and 78% of patients on the placebo arm used subsequent therapies that may prolong OS in metastatic CRPC. Abiraterone acetate was used as a subsequent therapy in 13% of patients on the abiraterone acetate arm and 44% of patients on the placebo arm.

Table 6: Overall Survival of Patients Treated with Either Abiraterone Acetate or Placebo in Combination with Corticosteroid in Study 2 (Intent-to-Treat Analysis)

Overall Survival | Abiraterone Acetate with Corticosteroid (N=546) | Placebo with Corticosteroid (N=542)
Deaths | 354 (65%) | 387 (71%)
Median survival (months); (95% CI) | 34.7; (3.7, 36.8) | 30.3; (28.7, 33.3)
p-value1 | 0.0033
Hazard ratio2 (95% CI) | 0.81 (0.70, 0.93)
1 p-value is derived from a log-rank test stratified by ECOG performance status score (0 vs. 1).
2 Hazard Ratio is derived from a stratified proportional hazards model. Hazard ratio <1 favors abiraterone acetate with prednisone.

Figure 2: Kaplan Meier Overall Survival Curves in Study 2

At the pre-specified rPFS analysis, 150 (28%) patients treated with abiraterone acetate with a corticosteroid and 251 (46%) patients treated with placebo with a corticosteroid had radiographic progression. A significant difference in rPFS between treatment groups was observed (Table 7and Figure 3).

Table 7: Radiographic Progression-free Survival of Patients Treated with Either Abiraterone Acetate or Placebo in Combination with Corticosteroid in Study 2 (Intent-to-Treat Analysis)

Radiographic Progression-free Survival | Abiraterone Acetate with Corticosteroid (N=546) | Placebo with Corticosteroid (N=542)
Progression or death | 150 (28%) | 251 (46%)
Median rPFS (months); (95% CI) | NR; (11.66, NR) | 8.28; (8.12, 8.54)
p-value1 | <0.0001
Hazard ratio2 (95% CI) | 0.425 (0.347, 0.522)
NR= Not Reached
1 p-value is derived from a log-rank test stratified by ECOG performance status score (0 vs. 1).
2 Hazard Ratio is derived from a stratified proportional hazards model. Hazard ratio <1 favors abiraterone acetate with prednisone.

Figure 3: Kaplan Meier Curves of Radiographic Progression-free Survival in Study 2 (Intent-to-Treat Analysis)

The primary efficacy analyses are supported by the following prospectively defined endpoints. The median time to initiation of cytotoxic chemotherapy was 25.2 months for patients in the abiraterone acetate arm and 16.8 months for patients in the placebo arm (HR=0.580; 95% CI: [0.487, 0.691], p<0.0001).

The median time to opiate use for prostate cancer pain was not reached for patients receiving abiraterone acetate and was 23.7 months for patients receiving placebo (HR=0.686; 95% CI: [0.566, 0.833], p=0.0001). The time to opiate use result was supported by a delay in patient reported pain progression favoring the abiraterone acetate arm.

16 HOW SUPPLIED/STORAGE AND HANDLING

Abiraterone acetate tablets, 125 mg

White to off-white, oval-shaped tablets debossed with “125 FP” on one side

120 tablets available in high-density polyethylene bottles with child resistant closure

NDC Number 51407-503-12

Storage and Handling

Store at 20oC to 25oC (68oF to 77oF); excursions permitted in the range from 15oC to 30oC (59oF to 86°F) [see USP Controlled Room Temperature].

Keep out of reach of children.

Based on its mechanism of action, Abiraterone Acetate may harm a developing fetus. Women who are pregnant or women who may be pregnant should not handle Abiraterone Acetate tablets if broken, crushed, or damaged without protection, e.g., gloves [see Use in Specific Populations (8.1)].

17 PATIENT COUNSELING INFORMATION

Advise the patient to read the FDA-approved patient labeling (Patient Information)

Hypokalemia, Fluid Retention, and Cardiovascular Adverse Reactions

- Inform patients that Abiraterone Acetate is associated with hypertension, hypokalemia, and peripheral edema that may lead to QT prolongation and Torsades de Pointes in patients who develop hypokalemia while taking Abiraterone Acetate. Advise patients that their blood pressure, serum potassium and signs and symptoms of fluid retention will be monitored clinically at least monthly. Advise patients to adhere to corticosteroids and to report symptoms of hypertension, hypokalemia, or edema to their healthcare provider [see Warnings and Precautions (5.1)].

Adrenocortical Insufficiency

- Inform patients that Abiraterone Acetate with methylprednisolone is associated with adrenal insufficiency. Advise patients to report symptoms of adrenocortical insufficiency to their healthcare provider [see Warnings and Precautions (5.2)].

Hepatotoxicity

- Inform patients that Abiraterone Acetate is associated with severe hepatotoxicity. Inform patients that their liver function will be monitored using blood tests. Advise patients to immediately report symptoms of hepatotoxicity to their healthcare provider [see Warnings and Precautions (5.3)].

Hypoglycemia

- Inform patients that severe hypoglycemia has been reported when abiraterone acetate was administered to patients with pre-existing diabetes who were receiving medications containing thiazolidinediones (including pioglitazone) or repaglinide – antidiabetic drugs. Advise patients with diabetes to monitor blood glucose levels during and after treatment with Abiraterone Acetate [see Warnings and Precautions (5.6)and Drug Interactions (7.2)].

Use in Combination with Radium Ra 223 Dichloride

- Advise patients that radium Ra 223 dichloride showed an increase in mortality and an increased rate of fracture when used in combination with abiraterone acetate plus a corticosteroid. Inform patients to speak with their healthcare provider about any other medications or treatment they are currently taking for prostate cancer [see Warnings and Precautions (5.4)].

Dosing and Administration

- Inform patients that Abiraterone Acetate tablets may not be interchangeable with other abiraterone acetate products due to different dosing and food effects [see Dosage and Administration (2.2)].
- Inform patients that Abiraterone Acetate is taken once daily with methylprednisolone twice daily and to not interrupt or stop either of these medications without consulting their healthcare provider [see Dosage and Administration (2.2)].
- Inform patients receiving GnRH therapy that they need to maintain this treatment during the course of treatment with Abiraterone Acetate [see Dosage and Administration (2.2)].
- Instruct patients to take Abiraterone Acetate tablets as a single dose once orally with or without food. Instruct patients to swallow tablets whole with water and not to crush or chew the tablets [see Dosage and Administration (2.2)].
- Inform patients that if they miss a dose of Abiraterone Acetate or methylprednisolone, they should take their normal dose the following day. If more than one daily dose is skipped, inform patients to contact their healthcare provider [see Dosage and Administration (2.2)].

Embryo-Fetal Toxicity

- Inform patients that Abiraterone Acetate may harm a developing fetus and can cause loss of pregnancy.
- Advise males with female partners of reproductive potential to use effective contraception during treatment and for 3 weeks after the last dose of Abiraterone Acetate [see Use in Specific Populations (8.1)].
- Advise females who are pregnant or women who may be pregnant not to handle Abiraterone Acetate tablets if broken, crushed, or damaged without protection, e.g., gloves [see Use in Specific Populations (8.1) and How Supplied/Storage and Handling (16)].

Infertility

- Advise male patients that Abiraterone Acetate may impair fertility [see Use in Specific Populations (8.3)].

Manufactured for:

Sun Pharmaceutical Industries Limited

Distributed by:

Sun Pharmaceutical Industries, Inc.

Cranbury, NJ 08512

Revised: 2022 July

Marketed by:
GSMS, Inc.
Camarillo, CA 93012 USA

PATIENT INFORMATION

< align="left" valign="middle" width="50%" /> < align="left" valign="middle" width="50%" />

PATIENT INFORMATION

< style="background-color: transparent;">Abiraterone Acetate

tablets

What is Abiraterone Acetate?

Abiraterone Acetate is a prescription medicine that is used along with methylprednisolone. Abiraterone Acetate is used to treat men with prostate cancer that has spread to other parts of the body and no longer responds to medical or surgical treatment that lowers testosterone.

It is not known if Abiraterone Acetate is safe and effective in females or children.

Before taking Abiraterone Acetate, tell your healthcare provider about all of your medical conditions, including if you:

- have heart problems
- have liver problems
- have diabetes
- have a history of adrenal problems
- have a history of pituitary problems
- are receiving any other treatment for prostate cancer
- are pregnant or plan to become pregnant. Abiraterone Acetate can cause harm to your unborn baby and loss of pregnancy (miscarriage). Females who are or may become pregnant should not handle Abiraterone Acetate tablets if broken, crushed, or damaged without protection, such as gloves.
- have a partner who is pregnant or may become pregnant.
  - Males who have female partners who are able to become pregnant should use effective birth control (contraception) during treatment with Abiraterone Acetate and for 3 weeks after the last dose of Abiraterone Acetate.
- are breastfeeding or plan to breastfeed. It is not known if Abiraterone Acetate passes into your breastmilk.

Tell your healthcare provider about all the medicines you take or treatments you receive,including prescription and over-the-counter medicines, vitamins, and herbal supplements. Abiraterone Acetate can interact with many other medicines.

You should not start or stop any medicine before you talk with the healthcare provider that prescribed Abiraterone Acetate.

Know the medicines you take. Keep a list of them with you to show to your healthcare provider and pharmacist when you get a new medicine.

How should I take Abiraterone Acetate?

- Take Abiraterone Acetate and methylprednisolone exactly as your healthcare provider tells you.
- Take your prescribed dose of Abiraterone Acetate 1 time a day. Take your prescribed dose of methylprednisolone 2 times a day.
- Abiraterone Acetate and other medicines that contain abiraterone acetate may not be the same.
  - Do notswitch between Abiraterone Acetate and other medicines that contain abiraterone acetate unless your healthcare provider tells you to.
  - Follow your healthcare provider’s instructions carefully if you are switching between and another medicine that contains abiraterone acetate.
  - Do not takeAbiraterone Acetate and other medicines that contain abiraterone acetate on the same day.
  - If you do not have enough Abiraterone Acetate to take your full dose or if you have any other questions about Abiraterone Acetate, talk with your healthcare provider or pharmacist.
- Your healthcare provider may change your dose of Abiraterone Acetate if needed.
- Do not change or stop taking your prescribed dose of Abiraterone Acetate or methylprednisolone without talking with your healthcare provider first.
- Take Abiraterone Acetate with or without food.
- Swallow Abiraterone Acetate tablets whole. Do not crush or chew tablets.
- Take Abiraterone Acetate with water.
- If you miss a dose of Abiraterone Acetate or methylprednisolone, take your prescribed dose the following day. If you miss more than 1 dose, tell your healthcare provider right away.
- If you are receiving gonadotropin-releasing hormone (GnRH) therapy, you should continue your therapy during treatment with Abiraterone Acetate and methylprednisolone.
- If you take too much Abiraterone Acetate, call your healthcare provider or go to the nearest hospital emergency room right away.
- Your healthcare provider will do blood tests to check for side effects.

What are the possible side effects of Abiraterone Acetate?

Abiraterone Acetate may cause serious side effects, including:

- High blood pressure (hypertension), low blood potassium levels (hypokalemia), fluid retention (edema), and irregular heartbeats can happen during treatment with Abiraterone Acetate.This can be life threatening. To decrease the chance of this happening, you must take methylprednisolone with Abiraterone Acetate exactly as your healthcare provider tells you. Your healthcare provider will check your blood pressure, do blood tests to check your potassium levels, and check for any signs and symptoms of fluid retention every month during treatment with Abiraterone Acetate.

Tell your healthcare provider if you get any of the following symptoms:

- dizziness
- fast or irregular heartbeats
- feel faint or lightheaded
- headache

- confusion
- muscle weakness
- pain in your legs
- swelling in your legs or feet

- Adrenal problemsmay happen if you stop taking methylprednisolone, get an infection, or are under stress.
- Severe liver problems.You may develop changes in liver function blood tests. Your healthcare provider will do blood tests to check your liver before treatment with Abiraterone Acetate and during treatment with Abiraterone Acetate. Liver failure may occur, which can lead to death. Tell your healthcare provider right away if you notice any of the following changes:
  - yellowing of the skin or eyes
  - darkening of the urine
  - severe nausea or vomiting
- Increased risk of bone fracture and deathwhen Abiraterone Acetate and methylprednisolone, is used in combination with a type of radiation called radium Ra 223 dichloride. Tell your healthcare provider about any other treatments you are taking for prostate cancer.
- Severe low blood sugar (hypoglycemia).Severe low blood sugar with Abiraterone Acetate can happen in people who have diabetes and take certain antidiabetic medicines. You and/or your healthcare provider should check your blood sugar levels regularly during treatment with Abiraterone Acetate and after you stop treatment. Your healthcare provider may also need to change the dose of your antidiabetic medicines. Signs and symptoms of low blood sugar may include:

- headache
- drowsiness
- weakness
- dizziness
- confusion

- irritability
- hunger
- fast heartbeat
- sweating
- feeling jittery

The most common side effects of Abiraterone Acetate include:

- feeling weak or tired
- joint swelling or pain
- swelling in your legs or feet
- hot flushes
- diarrhea
- vomiting
- cough
- high blood pressure
- shortness of breath

- urinary tract infection
- bruising
- low red blood cells (anemia)
- high blood cholesterol and triglycerides
- high blood sugar levels
- changes in liver function blood tests
- low blood potassium levels
- certain other abnormal blood tests

Abiraterone Acetate may cause fertility problems in males, which may affect the ability to father children. Talk to your healthcare provider if you have concerns about fertility.

These are not all the possible side effects of Abiraterone Acetate. Call your healthcare provider for medical advice about side effects. You may report side effects to FDA at 1-800-FDA-1088.

How should I store Abiraterone Acetate?

- Store Abiraterone Acetate at room temperature between 68°F to 77°F (20°C to 25°C).

Keep Abiraterone Acetate and all medicines out of the reach of children.

General information about the safe and effective use of Abiraterone Acetate.

Medicines are sometimes prescribed for purposes other than those listed in a Patient Information leaflet. Do not use Abiraterone Acetate for a condition for which it was not prescribed. Do not give Abiraterone Acetate to other people, even if they have the same symptoms that you have. It may harm them.

You can ask your healthcare provider or pharmacist for information about Abiraterone Acetate that is written for health professionals.

What are the ingredients in Abiraterone Acetate?

Active ingredient:abiraterone acetate.

Inactive ingredients:lactose monohydrate, microcrystalline cellulose, croscarmellose sodium, sodium lauryl sulfate, sodium stearyl fumarate, butylated hydroxyanisole, butylated hydroxytoluene.

Manufactured for Sun Pharmaceutical Industries Limited

Distributed by Sun Pharmaceutical Industries, Inc., Cranbury, NJ 08512

All rights reserved.

For more information, call Sun Pharmaceutical Industries, Inc at 1-800-818-4555 or go to https://gsms.us/

Marketed by:
GSMS, Inc.
Camarillo, CA 93012 USA

This Patient Information has been approved by the U.S. Food and Drug Administration Revised: 07/2022